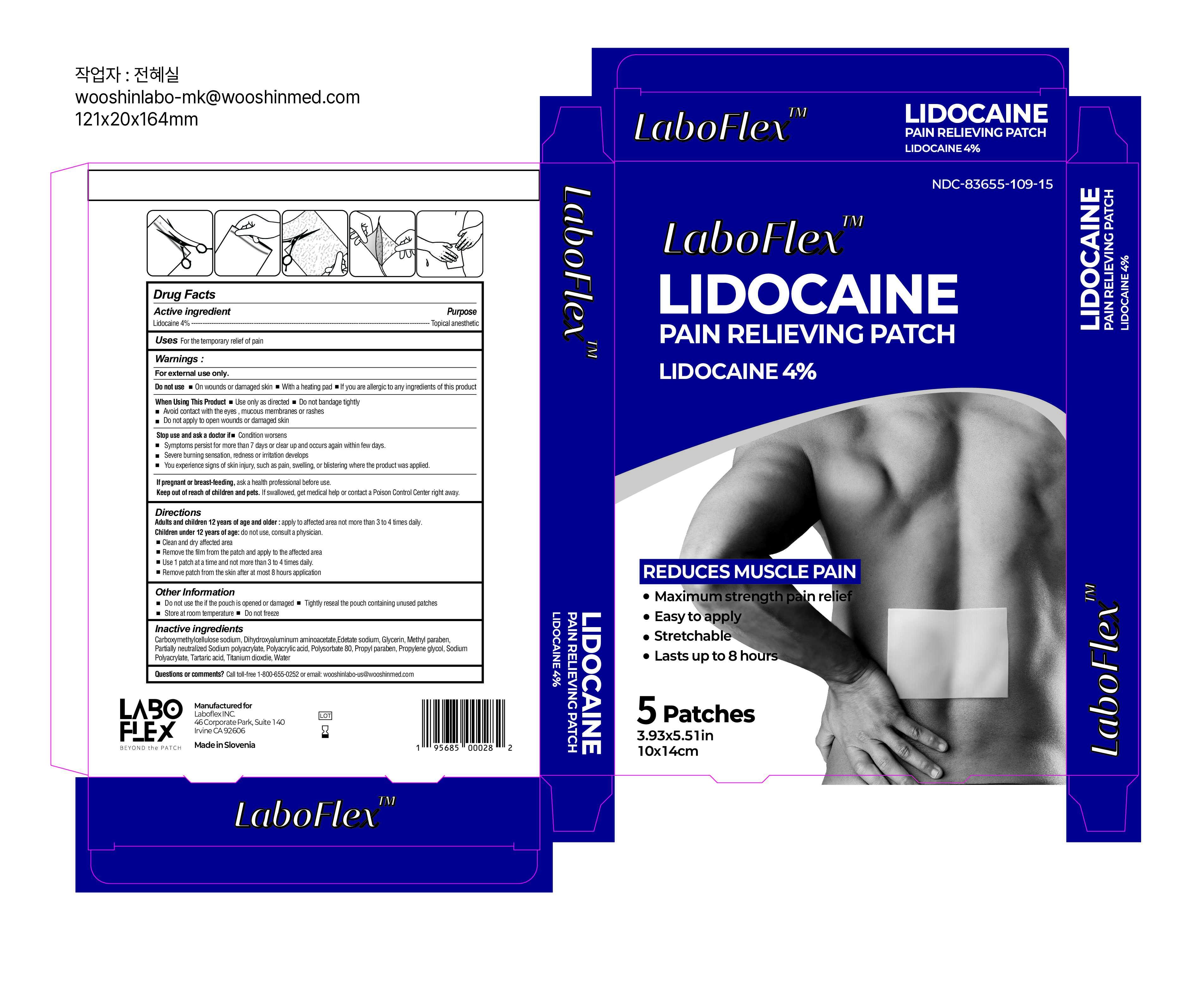 DRUG LABEL: LABOFLEX Lidocaine Pain Relieving Patch
NDC: 83655-109 | Form: PATCH
Manufacturer: Laboflex, Inc.
Category: otc | Type: HUMAN OTC DRUG LABEL
Date: 20250110

ACTIVE INGREDIENTS: LIDOCAINE 40 mg/1 g
INACTIVE INGREDIENTS: WATER; GLYCERIN; CARBOXYMETHYLCELLULOSE SODIUM, UNSPECIFIED FORM; PROPYLENE GLYCOL; TARTARIC ACID; POLYSORBATE 80; POLYACRYLIC ACID (250000 MW); SODIUM POLYACRYLATE (2500000 MW); TITANIUM DIOXIDE; DIHYDROXYALUMINUM AMINOACETATE ANHYDROUS; METHYLPARABEN; EDETATE SODIUM; PROPYLPARABEN

LABOFLEX Lidocaine Pain Relieving Patch - lidocaine 4%

Active ingredient

Lidocaine 4%

Inactive ingredients

Carboxymethylcellulose sodium, Dihydroxyaluminum aminoacetate, Edetate sodium, Glycerin, Lidocaine, Methyl paraben, Partially neutralized Sodium Polyacrylate, Polyacrylic acid, Polysorbate 80, Propyl paraben, Propylene glycol, Sodium Polyacrylate, Tartaric acid, Titanium dioxide, Water.

Directions:

Adults and children 12 years of age and older:apply to affected area not more than 3 to 4 times daily.

Children under 12 years of age: do not use, consult a physiciacn.

- clean and dry affected area
- remove the film from the patch and apply to the affected area
- Use 1 patch at a time and not more than 3 to 4 times daily.
- Remove patch from the skin after at most 8 hours application

Keep Out of Reach of Children.If swallowed, get medical help or contact a Poison Control Center right away.

If pregnant or breast feeding, ask a health professional before use.

Stop Use and Ask a Doctor if

Stop use and ask doctor if:

- Condition worsens
- Symptoms persist for more than 7 days or clear up and occur again within a few days
- Severe burning sensation, redness or irritation developss
- You experience signs of skin injury, such as pain, swelling, or blistering where the product was applied

When Using This Product

When using the product:

- use only as directed.
- do not bandage tightly
- Avoid contact with the eyes, mucous membranes or rashes
- do not apply to open wounds or damaged skin

Do not Use

- On wounds or damaged skin
- With a heantig pad
- If you are allergic to any ingredients of this product

Warning

For external use only

Uses

For the temporary relief of pain

Other information

- Do not use if the pouch is opened or damaged
- Tighlty reseal the pouch containing unused patches
- Store at room temperature
- Do not freeze
- This package is child-resistant

Purpose

Topical anesthetic